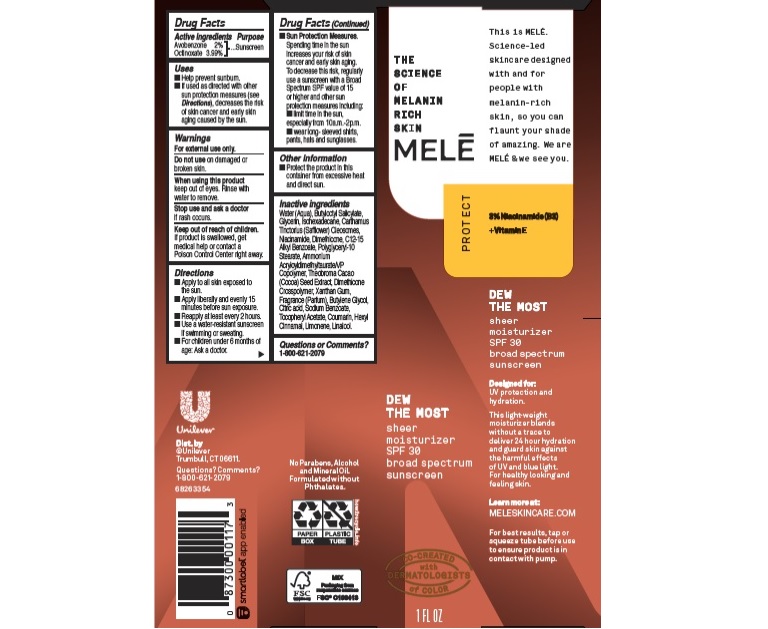 DRUG LABEL: Mele
NDC: 64942-1857 | Form: LOTION
Manufacturer: CONOPCO Inc. d/b/a Unilever
Category: otc | Type: HUMAN OTC DRUG LABEL
Date: 20241107

ACTIVE INGREDIENTS: OCTINOXATE 3.99 g/100 mL; AVOBENZONE 2 g/100 mL
INACTIVE INGREDIENTS: NIACINAMIDE; COUMARIN; .ALPHA.-HEXYLCINNAMALDEHYDE; COCOA; BUTYLOCTYL SALICYLATE; GLYCERIN; ISOHEXADECANE; CARTHAMUS TINCTORIUS SEED OLEOSOMES; WATER; POLYGLYCERYL-10 STEARATE; AMMONIUM ACRYLOYLDIMETHYLTAURATE/VP COPOLYMER; DIMETHICONE CROSSPOLYMER (450000 MPA.S AT 12% IN CYCLOPENTASILOXANE); XANTHAN GUM; BUTYLENE GLYCOL; CITRIC ACID MONOHYDRATE; SODIUM BENZOATE; .ALPHA.-TOCOPHEROL ACETATE; DIMETHICONE; LIMONENE, (+)-; LINALOOL, (+/-)-; ALKYL (C12-15) BENZOATE

Melē Dew The Most Sheer Moisturizer Sunscreen SPF 30

MELĒ DEW THE MOST SHEER MOISTURIZER SUNSCREEN SPF 30 - (sunscreen, avobenzone, octinoxate) lotion

Melē Dew The Most Sheer Moisturizer Sunscreen SPF 30

Drug Facts

Active ingredient
Avobenzone 2%
Octinoxate 3.99%

Purpose

Sunscreen

Uses

Help prevent sunburn
If used as directed with other sun protectionmeaseure (see Directions) decreases the risk of skin cancer and early skin aging caused by the sun

Warnings

For external use only
Do not use on damaged or broken skin
When using this product keep out of eyes. Rinse with water to remove
Stop use and ask a doctor if rash occurs

Keep out of reach of children
If product is swallowed, get medical help or contact a PoisonCcontrol Center right away.

Directions

Apply to all skin exposed to the sun
Apply liberally and evenly 15 minutes before sun exposure
Reapply at least every 2 hours
Use a water resistant sunscreen if swimming or sweating
Sun Protection Measures Spending time in the sun increases your risk of skin cancer and early skin aging. To decrease this rish, regularly use a sunscreen with a Broad Spectum SPF value of 15 or higher and other sun protection measures including

limit time in the sun, especiallu from 10a.m. - 2p.m.

wear long-sleeved shirts, pants, hats and sunglasses

Inactive ingredients

Water (Aqua), Butyloctyl Salicylate, Glycerin, Isohexadecane, Carthamus Tinctorius (Safflower) Oleosomes, Niacinamide, Dimethicone, C12-15 Alkyl Benzoate, Polyglyceryl-10 Stearate, Ammonium Acryloyldimethyltaurate/VP Copolymer, Theobroma Cacao (Cocoa) Seed Extract, Dimethicone Crosspolymer, Xanthan Gum, Fragrance (Parfum), Butylene Glycol, Citric Acid, Sodium Benzoate, Tocopheryl Acetate, Coumarin, Hexyl Cinnamal, Limonene. Linalool.

Questions or Comments?

1-800-621-2079